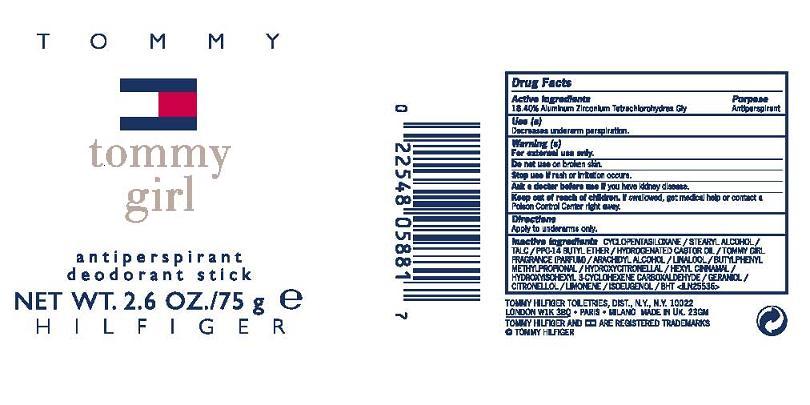 DRUG LABEL: TOMMY GIRL ANTIPERSPIRANT 
NDC: 64268-001 | Form: STICK
Manufacturer: TOMMY HILFIGER TOILETRIES
Category: otc | Type: HUMAN OTC DRUG LABEL
Date: 20110819

ACTIVE INGREDIENTS: ALUMINUM ZIRCONIUM TETRACHLOROHYDREX GLY  18.4 g/100 g
INACTIVE INGREDIENTS: CYCLOMETHICONE 5; STEARYL ALCOHOL; HYDROGENATED CASTOR OIL; ARACHIDYL ALCOHOL; TALC; PPG-14 BUTYL ETHER

ACTIVE INGREDIENT

ALUMINUM ZIRCONIUM TETRACHLOROHYDREX-GLY 18.4%

INACTIVE INGREDIENT

INACTIVE INGREDIENTS: CYCLOPENTASILOXANE [] STEARYL ALCOHOL [] TALC [] PPG-14 BUTYL ETHER [] HYDROGENATED CASTOR OIL [] ARACHIDYL ALCOHOL [] FRAGRANCE (PARFUM) [] LAURYL METHACRYLATE/GLYCOL DIMETHACRYLATE CROSSPOLYMER

PURPOSE: ANTIPERSPIRANT

INDICATIONS AND USAGE

USE: REDUCES UNDERARM WETNESS

WARNINGS:

- FOR EXTERNAL USE ONLY
- DO NOT USE ON BROKEN SKIN
- STOP USE IF IRRITATION OCCURS

ASK A DOCTOR BEFORE USE IF YOU HAVE KIDNEY DISEASE.

KEEP OUT OF REACH OF CHILDREN. IF SWALLOWED, GET MEDICAL HELP OR CONTACT A POISON CONTROL CENTER IMMEDIATELY.

DOSAGE AND ADMINISTRATION

DIRECTIONS: APPLY TO UNDERARMS ONLY

PACKAGE LABEL

PRINCIPAL DISPLAY PANEL:

TOMMY HILFIGER

TOMMY

GIRL

ANTIPERSPIRANT

DEODORANT

STICK

NT WT. 2.6 OZ./75 g

TOMMY HILFIGER TOILETRIES, DISTR

NY, NY 10022